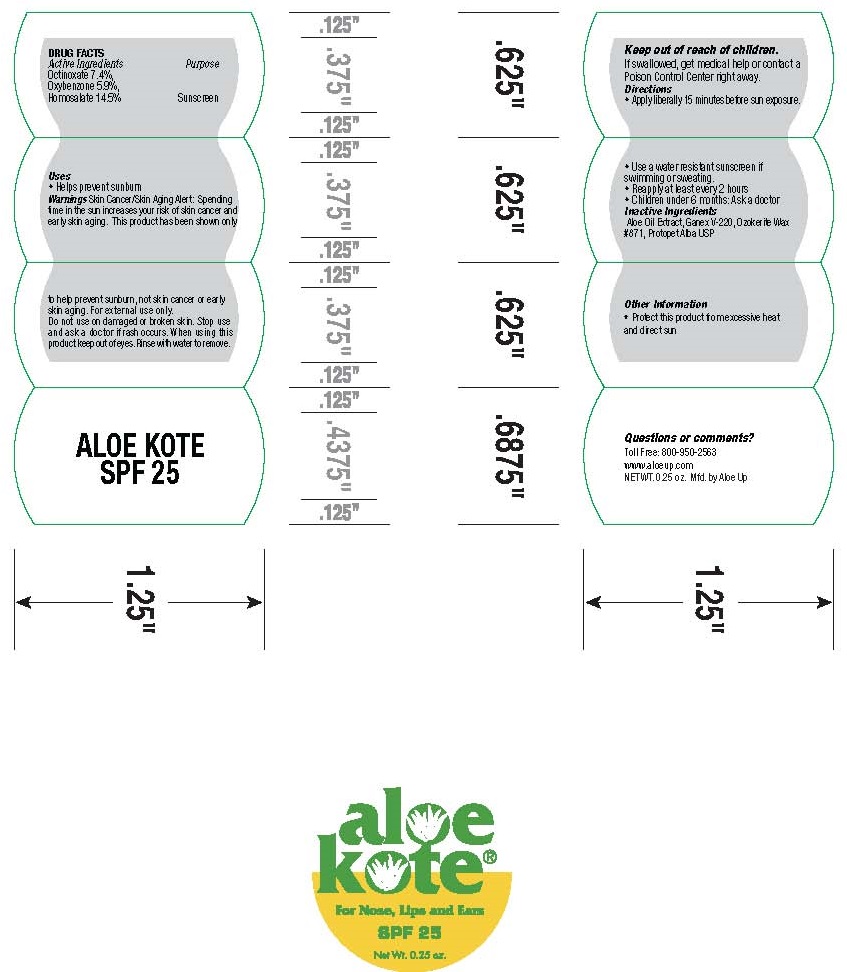 DRUG LABEL: ALOE KOTE
NDC: 61477-225 | Form: CREAM
Manufacturer: Aloe Care International, LLC
Category: otc | Type: HUMAN OTC DRUG LABEL
Date: 20260126

ACTIVE INGREDIENTS: OCTINOXATE 7.4 g/100 g; HOMOSALATE 14.5 g/100 g; OXYBENZONE 5.9 g/100 g
INACTIVE INGREDIENTS: ALOE VERA LEAF; EICOSYL POVIDONE; CERESIN; PETROLATUM

ALOE UP - ALOE KOTE SPF-25 (61477-225)

ACTIVE INGREDIENTS:

OCTINOXATE (7.4%)

OXYBENZONE (5.9%)

HOMOSALATE (14.5%)

PURPOSE:

SUNSCREEN

USES

HELPS PREVENT SUNBURN.

DIRECTIONS:

- APPLY LIBERALLY 15 MINUTES BEFORE SUN EXPOSURE.
- USE A WATER RESISTANT SUNSCREEN IF SWIMMING OR SWEATING.
- REAPPLY AT LEAST EVERY 2 HOURS.
- CHILDREN UNDER 6 MONTHS: ASK A DOCTOR.

KEEP OUT OF REACH OF CHILDREN. IF SWALLOWED, GET MEDICAL HELP OR CONTACT A POISON CONTROL CENTER RIGHT AWAY.

WARNINGS:

Skin Cancer/Skin Aging Alert: Spending time in the sun increases your risk of skin cancer and early skin aging. This product has been shown only to help prevent sunburn, not skin cancer or early skin aging. For external use only. Do not use on damaged or broken skin. Stop use and ask a doctor if rash occurs. When using this product keep out of eyes. Rinse with water to remove.

INACTIVE INGREDIENTS

Aloe Oil Extract, Ganex V-220, Ozokerite Wax #871, Protopet Alba USP

OTHER INFORMATION

• Protect this product from excessive heat and direct sun

Questions or comments?

Toll Free 800-950-2563

www.aloeup.com